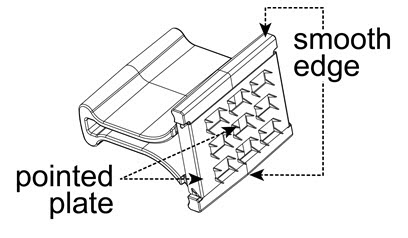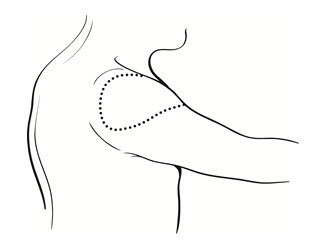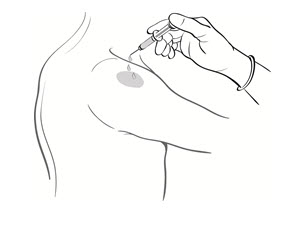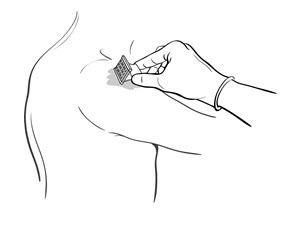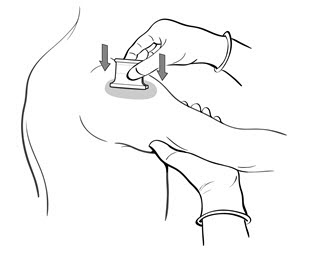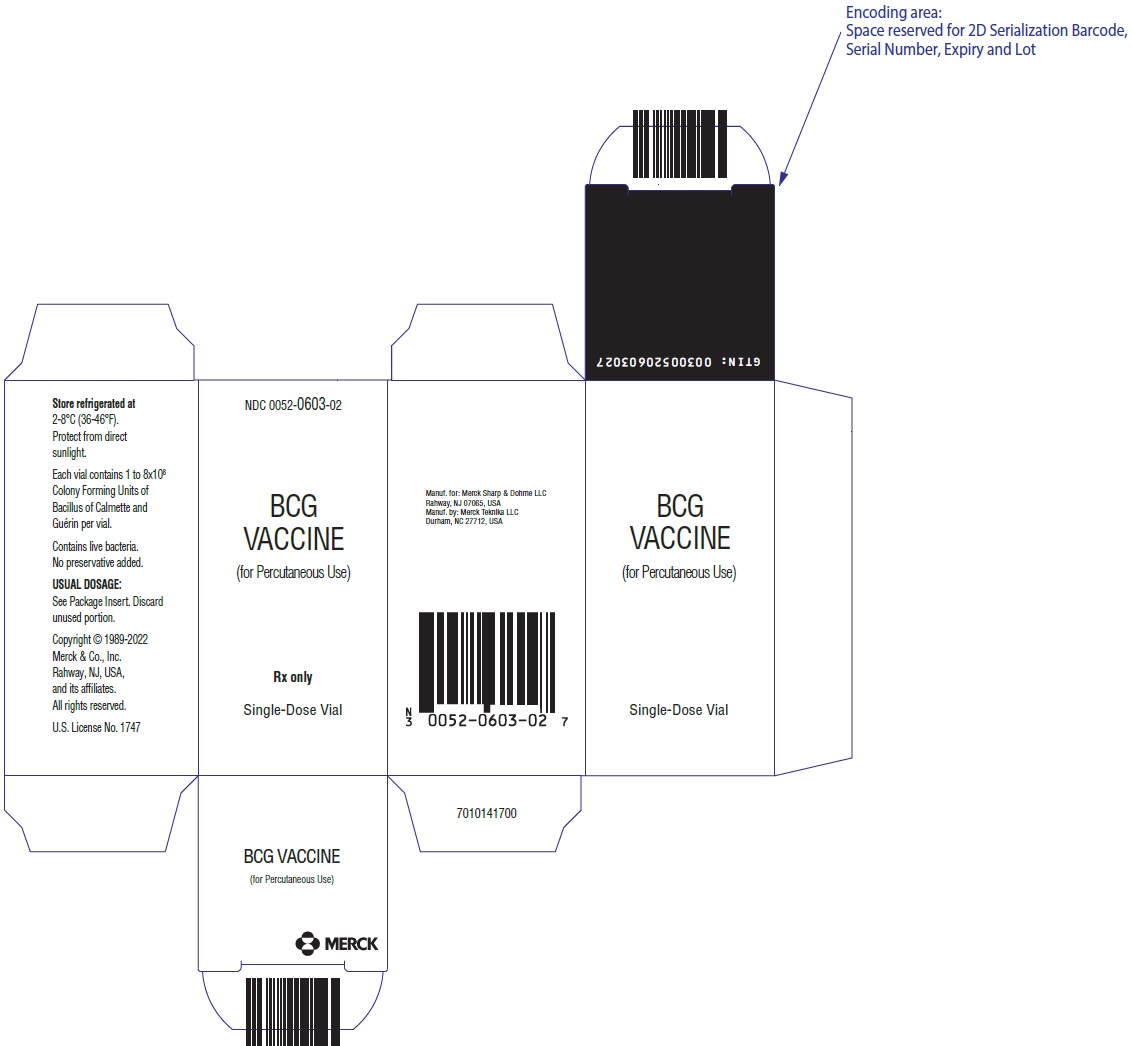 DRUG LABEL: BCG VACCINE
NDC: 0052-0603 | Form: INJECTION, POWDER, LYOPHILIZED, FOR SOLUTION
Manufacturer: Merck Sharp & Dohme LLC
Category: other | Type: VACCINE LABEL
Date: 20241011

ACTIVE INGREDIENTS: BACILLUS CALMETTE-GUERIN SUBSTRAIN TICE LIVE ANTIGEN 50 mg/1 1
INACTIVE INGREDIENTS: LACTOSE, UNSPECIFIED FORM; Water; glycerin; asparagine; citric acid monohydrate; potassium phosphate, unspecified form; MAGNESIUM SULFATE, UNSPECIFIED FORM; ferric ammonium citrate

BCG VACCINE
(FOR PERCUTANEOUS USE)

DESCRIPTION

BCG VACCINE for percutaneous use is an attenuated, live culture preparation of the Bacillus of Calmette and Guerin (BCG) strain of Mycobacterium bovis.{1} The TICE® strain used in this BCG VACCINE preparation was developed at the University of Illinois from a strain originated at the Pasteur Institute.

The medium in which the TICE® BCG organism is grown for preparation of the freeze-dried cake is composed of the following ingredients: glycerin, asparagine, citric acid, potassium phosphate, magnesium sulfate, and iron ammonium citrate. The final preparation prior to freeze drying also contains lactose. The freeze-dried BCG preparation is delivered in vials, each containing 1 to 8 × 10^8 colony forming units (CFU) of BCG which is equivalent to approximately 50 mg wet weight. Determination of in-vitro potency is achieved through colony counts derived from a serial dilution assay. Intradermal guinea pig testing is also used as an indirect measure of potency.

Reconstitution requires addition of Sterile Water for Injection, USP at 4-25°C (39-77°F). For an adult dosage, 1 mL of Sterile Water for Injection, USP, should be added to one single-dose vial of vaccine. For a pediatric dosage, 2 mL of Sterile Water for Injection, USP, should be added to one single-dose vial of vaccine (see DOSAGE AND ADMINISTRATION).

No preservatives have been added.

CLINICAL PHARMACOLOGY

Tuberculosis (TB) is primarily an airborne communicable disease caused by the bacterium, Mycobacterium tuberculosis.

Tuberculosis is an important global public health problem with an estimated 8–10 million cases and 2–3 million deaths occurring each year.{2} The control of TB in the United States has been a constant challenge particularly with the resurgence in TB in the late 1980s and the early 1990s. In the United States, TB had declined approximately 6% per year since nationwide reporting began in 1953. However, in 1985 there was a 1.1% increase over the previous year. This upward trend continued through 1992, when the incidence was 10.5 cases per 100,000 population. In 1993, there was a 5.2% decrease over 1992 with a rate of 9.8 cases per 100,000 population.{3} In 1997, the total TB cases reported was 19,855 or 7.4 cases per 100,000 people. This incidence rate represented the fifth consecutive year that number of reported TB cases had declined and a 26% decrease since the peak in 1992.{4}

In the 1990s, drug-resistant TB also became a significant public health concern. During the period of 1993–1996, in the United States, 13.1% of TB patients were infected with TB strains that were resistant to at least one drug used as first-line treatment for TB (isoniazid, rifampin, pyrazinamide, ethambutol, and streptomycin) and 2.2% of TB patients were infected with TB strains that were multiple drug resistant (MDR as defined by resistance to both isoniazid and rifampin). Cases of MDR-TB were reported from 42 states and Washington D.C. during this time period.{5}

Most persons infected with M. tuberculosis remain infected for many years by developing latent infections. Active TB will reactivate during the lifetime of 5–15% of infected patients who are immunocompetent. In general, active TB is fatal for about 50% of persons who have not been treated.{3} The greatest known risk factor for developing active TB disease is immunodeficiency, particularly if caused by coinfection with HIV.{4} Persons infected with HIV are estimated to be over one hundred times as likely as uninfected persons to develop TB, primarily as a result of reactivation of a latent TB infection.{6} Other groups at high risk for developing TB include foreign-born individuals and persons in institutional settings such as correctional facilities, shelters for the homeless, and nursing homes.

Although over 2 billion people have been immunized with BCG, and it is currently an officially recommended vaccine in more than 180 countries, excluding the U.S., the efficacy of BCG as a vaccine against tuberculosis remains controversial. Prospective vaccine efficacy trials have shown that the protective benefit of BCG (various strains from different manufacturers) against clinical TB was variable, ranging from 0–80%.{7} A recent meta-analysis of data from 14 prospective trials and 12 case control studies concluded that the overall protective effect of BCG against tuberculosis infection was 50%.{8} The reasons for the wide range of effectiveness seen in these studies are unknown but may be attributed to the following: vaccination was not allocated randomly in observational studies; there were differences in BCG strains, methods, and routes of administration; and there were differences in the characteristics of the populations and environments in which the vaccines were studied.{9} Despite the conflicting results concerning prevention of pulmonary tuberculosis, it is widely acknowledged that immunization of infants with BCG lowers the risk of disseminated complications of this disease. Estimates in areas where BCG vaccination is performed at birth indicate that the effectiveness of BCG in preventing childhood TB meningitis or miliary TB exceeds 70%.{10-15}

In a prospective trial using the TICE® strain of BCG VACCINE, Rosenthal, et al., studied 1,716 vaccinated and 1,665 non-vaccinated infants, all born at the Cook County Hospital in Chicago and followed for 12–23 years. The diagnosis of tuberculosis was made following a review of chest X-ray results and clinical findings. There were 17 cases of tuberculosis among the vaccinated (0.43/1,000/yr) and 65 cases in the nonvaccinated (1.7/1,000/yr); this is a reduction of 75% (p<0.001) in cases of tuberculosis. One death was attributed to tuberculosis in the vaccinated group with 6 deaths in the controls, or a reduction of 83%. There were 639 families in which there was a sibling in both the control and vaccination groups. Eight of the 790 vaccinated subjects developed tuberculosis as compared with 30 of the 945 controls (p<0.001). Thirteen cases of nonfatal tuberculosis developed in the control group that were 2 years of age and under, with none in the vaccinated group.

There were 3 deaths from tuberculosis in the control group that were less than 2.5 years of age (all had miliary tuberculosis with meningitis), with one death in the vaccinated group (meningitis). The infant who died in the vaccinated group had not converted to a positive purified protein derivative (PPD) skin test at 6 months of age and was never subsequently revaccinated. Following a single vaccination, 99.3% of all infants studied became PPD positive, with 84.2% still being positive after 8 years.{16}

In a 1995 study of vaccine potency, 26 tuberculin negative subjects were vaccinated with BCG VACCINE (TICE® strain) and subsequent tuberculin conversion was monitored. Conversion from a negative to a positive skin test may be considered a surrogate indicator of potency and immunization efficacy of BCG Vaccines; however, the correlation between PPD conversion and vaccine effectiveness has not been established. Twenty-four (24) subjects returned for follow-up testing with PPD 10 tuberculin units (10 TU) 8 weeks after vaccination. Twenty-two (22) of the 24 subjects converted to positive (skin test reading >5mm induration at 48 hours) and 2 remained negative. The conversion rate was 92% and the average positive skin test reading was 15.5mm in induration.{17}

In a second study, 22 volunteers between the ages of 18 and 40 who were not health care workers, were not foreign born, were HIV negative, and were negative responders to a 10 TU PPD skin test were vaccinated with the standard dose of BCG VACCINE (TICE® strain). Eight weeks after vaccination the subjects returned for a 10 TU skin test. Twenty-one (21) out of 22 converted to PPD positive at a level greater than 5mm for a skin test conversion rate of 95%.{17}

INDICATIONS AND USAGE

BCG VACCINE (TICE® strain) is indicated for the prevention of tuberculosis in persons not previously infected with M. tuberculosis who are at high risk for exposure. As with any vaccine, immunization with BCG VACCINE may not protect 100% of susceptible individuals.

The Advisory Committee on Immunization Practices (ACIP) and the Advisory Committee for the Elimination of Tuberculosis has recommended that BCG vaccination be considered in the following circumstances.{3}

TB Exposed Tuberculin Skin Test-Negative Infants and Children

BCG vaccination is recommended for infants and children with negative tuberculin skin tests who are (a) at high risk of intimate and prolonged exposure to persistently untreated or ineffectively treated patients with infectious pulmonary tuberculosis and who cannot be removed from the source of exposure and cannot be placed on long-term primary preventive therapy, or (b) continuously exposed to persons with infectious pulmonary tuberculosis who have bacilli resistant to isoniazid and rifampin, and the child cannot be separated from the presence of the infectious patient.{3}

TB Exposed Health Care Workers (HCW) in High Risk Settings

BCG vaccination of HCWs should be considered on an individual basis in settings where (a) a high percentage of TB patients are infected with M. tuberculosis strains resistant to both isoniazid and rifampin, (b) transmission of such drug resistant M. tuberculosis strains to HCWs and subsequent infection are likely, and (c) comprehensive TB infection control precautions have been implemented and have not been successful. Vaccination should not be required for employment or for assignment of HCWs in specific work areas. HCWs considered for BCG vaccination should be counseled regarding the risks and benefits associated with both BCG vaccinations and TB preventive therapy.{3}

Exposed Health Care Workers in Low Risk Settings

BCG vaccination is not recommended for HCWs in settings in which the risk for M. tuberculosis transmission is low.{3}

CONTRAINDICATIONS

BCG VACCINE for prevention of tuberculosis should not be given to persons (a) whose immunologic responses are impaired because of HIV infections, congenital immunodeficiency such as chronic granulomatous disease or interferon gamma receptor deficiency, leukemia, lymphoma, or generalized malignancy or (b) whose immunologic responses have been suppressed by steroids, alkylating agents, antimetabolites, or radiation.{3} BCG VACCINE should not be administered to HIV-infected or immunocompromised infants, children, or adults.

Prior to administration, the possibility of allergic reactions should be assessed. Allergy to any component of BCG VACCINE or an anaphylactic or allergic reaction to a previous dose of BCG VACCINE are contraindications for vaccination.

BCG VACCINE is not a vaccine for the treatment of active tuberculosis.

BCG VACCINE should not be used in infants, children, or adults with severe immune deficiency syndromes. Children with a family history of immune deficiency disease should not be vaccinated; if they are, an infectious disease specialist should be consulted and anti-tuberculous therapy administered if clinically indicated.{18}

WARNINGS

Administration should be by the percutaneous route with the multiple puncture device as described below. DO NOT INJECT INTRAVENOUSLY, SUBCUTANEOUSLY, INTRAMUSCULARLY, OR INTRADERMALLY.

Although BCG vaccination often results in local adverse effects, serious or long-term complications are rare. Reactions that can be expected after vaccination include moderate axillary or cervical lymphadenopathy and induration and subsequent pustule formation at the injection site; these reactions can persist for as long as 3 months after vaccination. More severe local reactions include ulceration at the vaccination site, regional suppurative lymphadenitis with draining sinuses, and caseous lesions or purulent drainage at the puncture site; these manifestations might occur within the 5 months after vaccination and could persist for several weeks.

Acute, localized irritative toxicities of BCG may be accompanied by systemic manifestations, consistent with a "flu-like" syndrome. Systemic adverse effects of 1–2 days' duration such as fever, anorexia, myalgia, and neuralgia, often reflect hypersensitivity reactions. However, symptoms such as fever of 103°F or greater, or acute localized inflammation persisting longer than 2–3 days suggest active infections, and evaluation for serious infectious complication should be considered. If a BCG infection is suspected, the physician should consult with an infectious disease expert before therapy is initiated. Treatment should be started without delay. In patients who develop persistent fever or experience an acute febrile illness consistent with BCG infection, two or more antimycobacterial agents should be administered while diagnostic evaluation, including cultures, is conducted. Negative cultures do not necessarily rule out infection. Physicians or persons caring for patients that use this product should be familiar with the literature on prevention, diagnosis, and treatment of BCG-related complications and, when appropriate, should consult an infectious disease specialist or other physician with experience in the diagnosis and treatment of mycobacterial infections.

The most serious complication of BCG vaccination is disseminated BCG infection. BCG osteitis affecting the epiphyses of the long bones, particularly the epiphyses of the leg, can occur from 4 months to 2 years after vaccination. Fatal disseminated BCG disease has occurred at a rate of 0.06–1.56 cases per million doses of vaccine administered; these deaths occurred primarily among immunocompromised persons.{3} The appropriate therapy for systemic BCG infections is discussed in the ADVERSE REACTIONS section.

PRECAUTIONS

General

BCG VACCINE contains live bacteria and should be used with aseptic technique. To avoid cross-contamination, parenteral drugs should not be prepared in areas where BCG VACCINE has been in use.{19} A separate sterile multiple puncture device must be used for each patient and appropriately discarded after use. All equipment, supplies and receptacles in contact with BCG VACCINE should be handled and disposed of as biohazardous (see DOSAGE AND ADMINISTRATION).

BCG VACCINE administration should not be attempted in individuals with severe immune deficiency disease. BCG VACCINE should be administered with caution to persons in groups at high risk for HIV infection.

A review of each patient's immunization records to include history on reactions to immunizations should be completed prior to vaccination. All precautions should be taken for the prevention of allergic or any other side reactions, including understanding the use of the biological and the nature of the adverse reactions that may follow its use. Epinephrine injection (1:1000) for the control of immediate allergic reactions must be available should an acute anaphylactic reaction occur.

Vaccination is recommended only for those who are tuberculin negative to a recent skin test with 5 TU.

After BCG vaccination, it is usually not possible to clearly distinguish between a tuberculin reaction caused by persistent post-vaccination sensitivity and one caused by a virulent suprainfection. Caution is advised in attributing a positive skin test to BCG vaccination. A sharp rise in the tuberculin reaction since the latest test should be further investigated (except in the immediate post-vaccination period).

Information for Patients

Before administration of BCG VACCINE, health care personnel should inform patients or guardians of the benefits and risks of immunization and inquire about the health status of the patient. Health care workers considering BCG vaccination should be counseled regarding the risks and benefits associated with both BCG vaccination and TB preventive therapy. They should be informed about (a) the variable data concerning the efficacy of BCG vaccination, (b) the interference with the diagnosis of newly acquired M. tuberculosis infections in BCG-vaccinated persons, and (c) the potential serious complications associated with BCG vaccination of immunocompromised individuals. Health care workers should be informed about (a) the lack of data regarding the efficacy of preventive therapy for MDR-TB infections and (b) the risks of drug toxicity associated with multi-drug preventive therapy regimens.

Following BCG vaccination, no dressing is required; however, it is recommended that the site be loosely covered and kept dry for 24 hours. The vaccination site should be kept clean until the local reaction has disappeared. The patient should be advised that the vaccine contains live organisms. Although the vaccine will not survive in a dry state for long, infection of others is possible. Following vaccination with BCG, initial skin lesions usually appear within 10–14 days and consist of small red papules at the vaccination site. The papules reach a maximum diameter (about 3 mm) after 4 to 6 weeks, after which they may scale and slowly subside. Six months afterwards there is usually no visible sign of the vaccination, though on occasion, a faintly discernible pattern of the points from the multiple puncture device may be visible. On individuals whose skin tends to form keloids, there may be slightly more visible evidence of the vaccination. Any unusual adverse reactions should be reported to the health care provider.

Patients may experience "flu-like" symptoms for 24–48 hours following BCG vaccination. However, the patient should consult with their physician immediately if they experience fever of 103°F or greater, or acute local reactions persisting longer than 2–3 days.

Laboratory Tests

BCG vaccination results in tuberculin skin test reactivity. Tuberculin skin test reactivity as a result of BCG vaccination cannot be readily differentiated from reactivity following exposure to tuberculosis. BCG vaccination should not be administered to individuals with a positive tuberculin skin test.

Prior administration of BCG vaccine has not been associated with a positive interferon gamma release assay (IGRA) test, which are indirect tests for M. tuberculosis infection (including disease) and are intended for use in conjunction with risk assessment, radiography and other medical and diagnostic evaluations.{20,21}

Drug Interactions

Antimicrobial or immunosuppressive agents may interfere with the development of the immune response and should be used only under medical supervision.

Since BCG is a live vaccine, the immune response to the vaccine might be impaired if administered within 30 days of another live vaccine. However, no evidence exists for currently available vaccines to support this concern. Whenever possible, live vaccines administered on different days should be administered at least 30 days apart.{22}

Carcinogenesis, Mutagenesis, Impairment of Fertility

BCG VACCINE has not been evaluated for carcinogenic, mutagenic potentials or impairment of fertility.

Pregnancy

Animal reproduction studies have not been conducted with BCG VACCINE. It is also not known whether BCG VACCINE can cause fetal harm when administered to a pregnant woman or can affect reproductive capacity. Although no harmful effects to the fetus have been associated with BCG VACCINE, its use is not recommended during pregnancy.{3}

Nursing Mothers

It is not known whether BCG is excreted in human milk. Because many drugs are excreted in human milk and because of the potential for serious adverse reactions from BCG in nursing infants, a decision should be made whether to discontinue nursing or not to vaccinate, taking into account the importance of tuberculosis vaccination to the mother.

Pediatric Use

See Treatment and Schedule under DOSAGE AND ADMINISTRATION section. Precautions should be taken with respect to infants vaccinated with BCG and exposed to persons with active tuberculosis.{23}

Geriatric Use

Clinical studies of BCG VACCINE did not include sufficient numbers of subjects aged 65 and over to determine whether they respond differently from younger subjects. Other reported clinical experience has not identified differences in response between elderly and younger patients. An intact immune system is a prerequisite for BCG vaccination. If the immune status of an elderly patient, or any patient, is in question, the BCG vaccination should be held until the immune status of the patient has been evaluated.

ADVERSE REACTIONS

Although BCG vaccination often causes local reactions, serious or long-term complications are rare.{3} Reactions that can be expected after vaccination include moderate axillary or cervical lymphadenopathy and induration and subsequent pustule formation at the injection site; these reactions can persist for as long as 3 months after vaccination. More serious local reactions include ulceration at the vaccination site, regional suppurative lymphadenitis with draining sinuses, and caseous lesions or purulent draining at the puncture site. These manifestations might occur up to 5 months after vaccination and could persist for several weeks. The intensity and duration of the local reaction depends on the depth of penetration of the multiple puncture device and individual variations in patients' tissue reactions. Slight tenderness at the puncture site may be encountered as well as some itching. The initial skin lesions usually appear within 10–14 days and consist of small red papules at the site. The papules reach maximum diameter (about 3 mm) after 4 to 6 weeks, after which they may scale and then slowly subside.

The most serious complication of BCG vaccination is disseminated BCG infection.{24,25} The most frequent disseminated infection is BCG osteomyelitis (0.01 to 43 cases per million doses of vaccine administered) which usually occurs 4 months to 2 years after vaccination. Fatal disseminated BCG infection has occurred at a rate of 0.06–1.56 cases per million doses; these deaths occurred primarily among immunocompromised persons.

BCG Vaccination of Individuals Infected with HIV

The safety of BCG vaccination in HIV-infected adults and children, including infants, has not been determined by controlled or large studies. This is a concern because of the association between disseminated BCG infection and underlying immunosuppression. Individuals with HIV infection should not receive the BCG VACCINE.{3}

Treatment of Adverse Reactions

If a systemic BCG infection occurs, an infectious disease expert should be consulted and anti-tuberculosis therapy should be initiated. Since BCG strains are resistant to pyrazinamide, this antibiotic should not be used.

Reporting of Adverse Reactions

All suspected adverse reactions to BCG vaccination should be reported to Merck Sharp & Dohme LLC, Rahway, NJ USA at 1-877-888-4231 and to the Vaccine Adverse Event Reporting System (VAERS); telephone 1-800-822-7967. These reactions occasionally could occur more than 1 year after vaccination.

OVERDOSAGE

Accidental overdosages if treated immediately with anti-tuberculous drugs have not led to complications.{26} If the vaccination response is allowed to progress it can still be treated successfully with anti-tuberculous drugs but complications can include regional adenitis, lupus vulgaris, subcutaneous cold abscesses, ocular lesions, and others.{27}

DOSAGE AND ADMINISTRATION

Preparation of Agent

The preparation of the BCG VACCINE suspension should be done using aseptic technique. To avoid cross-contamination, parenteral drugs should not be prepared in areas where BCG VACCINE has been prepared. A separate area for the preparation of the BCG VACCINE suspension is recommended. All equipment, supplies and receptacles in contact with BCG VACCINE should be handled and disposed of as biohazardous. The pharmacist or individual responsible for mixing the agent should wear gloves and take precautions to avoid contact of BCG with broken skin. If preparation cannot be performed in a biocontainment hood, then a mask and gown should be worn to avoid inhalation of BCG organisms and inadvertent exposure to broken skin.

Using aseptic methods, 1 mL of Sterile Water for Injection, USP at 4-25°C (39-77°F), is added to one vial of vaccine (see Pediatric Dose below for pediatric use). Gently swirl the vial until a homogenous suspension is obtained. Avoid forceful agitation which may cause clumping of the mycobacteria.

Persons administering vaccines should take necessary precautions to minimize risk for spreading disease. Hands should be washed before each new patient is seen. Syringes and needles used for applications must be sterile and preferably disposable to minimize the risk of contamination. A separate needle and syringe should be used for each application. Disposable needles and the multiple puncture device should be discarded as biohazardous waste in labeled, puncture-proof containers to prevent inadvertent needlestick injury or reuse.{22} After use, any unused vaccine and all materials exposed to the product should be immediately placed in a biohazard container and disposed of in an appropriate manner.

Reconstituted vaccine should be kept refrigerated, protected from exposure to direct sunlight, and used within 2 hours. Freezing of the reconstituted product is not recommended. Discard unused portion.

Note: DO NOT filter the contents of the BCG VACCINE vial. Precautions should be taken to avoid exposing the BCG VACCINE to direct sunlight. Bacteriostatic solutions must be avoided. Parenteral drug products should be inspected visually for particulate matter and discoloration prior to administration, whenever solution and container permit. Reconstitution should result in a uniform suspension of the bacilli.

Treatment and Schedule

BCG vaccination is reserved for persons who have a reaction of less than 5mm induration after skin testing with 5 TU of PPD tuberculin. The preferred method of skin testing is the Mantoux tuberculin skin-test using 0.1 mL of 5 tuberculin units (TU) of PPD.{3} It is recommended that a Mantoux skin-test be performed prior to BCG vaccination to demonstrate the absence of tuberculous infection.

The vaccine is to be administered after fully explaining the risks and benefits to the vaccinee, parent, or guardian. BCG vaccination should not be given to individuals previously infected with M. tuberculosis. The vaccine is administered percutaneously utilizing a sterile, single-use multiple puncture device. The multiple puncture device consists of a plastic holder for a thin, wafer-like stainless steel plate from which 36 points protrude (Figure 1). After the vaccine is prepared, the skin site is cleansed with an alcohol or acetone sponge and allowed to dry thoroughly.

Figure 1

1. Administer the vaccine in the deltoid region (Figure 2). Position the arm to maintain a horizontal surface where the vaccine is to be placed.

Figure 2

2. Drop the immunizing dose of 0.2–0.3 mL of BCG VACCINE from the syringe and needle onto the cleansed surface of the skin (Figure 3) and spread over a 1" by 2" area using the smooth edge of the multiple puncture device (Figure 4).

Figure 3
Figure 4

3. Grasp the arm firmly from underneath, tensing the skin. Center the multiple puncture device over the vaccine and apply firm downward pressure such that the device points are well buried in the skin (Figure 5).

Figure 5

4. Maintain pressure for 5 seconds. Do not "rock" the device. Release the pressure underneath the arm and remove the device. In a successful procedure the points puncture the skin. If the points do not puncture the skin, the puncture procedure must be repeated.
5. After successful puncture, spread vaccine as evenly as possible over the puncture area with the smooth edge of the device (Figure 4). An additional 1–2 drops of BCG VACCINE may be added to ensure a very wet vaccination site.
6. Use the multiple puncture device once and discard in a standard biohazardous sharps container.
7. Loosely cover the site and keep dry for 24 hours.
8. Advise the patient that the vaccine contains live organisms. Although the vaccine will not survive in a dry state for long, infection of others is possible.

Tuberculin reactivity resulting from BCG vaccination should be documented. A vaccinated person should be tuberculin skin tested 2–3 months after BCG administration, and the test results, in millimeters of induration, should be recorded in the person's medical record.{9} Vaccination should be repeated for those who remain tuberculin negative to 5 TU of tuberculin after 2–3 months.

Pediatric Dose

Do not administer INTRAVENOUSLY, SUBCUTANEOUSLY, INTRAMUSCULARLY, OR INTRADERMALLY. Administer the vaccine in the deltoid region.

In infants less than 1 month old, the dosage of BCG VACCINE should be reduced by one-half, by using 2 mL of Sterile Water for Injection, USP at 4-25°C (39-77°F) when reconstituting. If a vaccinated infant remains tuberculin negative to 5 TU on skin testing, and if indications for vaccination persist, the infant should receive a full dose after 1 year of age.

HOW SUPPLIED

BCG VACCINE is supplied in a box of one single-dose vial of BCG. Each vial contains 1 to 8 × 10^8 CFU, which is equivalent to approximately 50 mg (wet weight), as lyophilized (freeze-dried) powder, NDC 0052-0603-02.

Multiple puncture devices may be obtained separately from the Order Management Center, Merck Sharp & Dohme LLC, 351 North Sumneytown Pike, North Wales, PA 19454-2505, Telephone number: 800-637-2579.

Storage

The intact vials of BCG VACCINE should be stored refrigerated at 2-8°C (36-46°F).

This agent contains live bacteria and should be protected from direct sunlight. The product should not be used after the expiration date printed on the label.

REFERENCES

1. Guerin C: The history of BCG. In: Rosenthal SR (ed): BCG VACCINE: Tuberculosis-Cancer. Littleton, MA, PSG Publishing Co., Inc. 1980; pp. 35-43.
2. Enarson, D, Murray, JF. Global Epidemiology of Tuberculosis. In: Rom, WN, Garay, SM (eds.); Tuberculosis. Boston, Little Brown and Company; 1996; pp. 57-76.
3. Centers for Disease Control and Prevention. The Role of BCG VACCINE in the Prevention and Control of Tuberculosis in the United States. MMWR 45(RR-4):1-18, 1996.
4. Centers for Disease Control and Prevention. Tuberculosis Morbidity – United States, 1998. MMWR 47(13):253-257.
5. Moore M, Ornarato IM, McCray E, Castro KG. Trends in Drug-Resistant Tuberculosis in the United States, 1993-1996. JAMA 1997;278:833-837.
6. Gordin FM, Matts JP, Miller C, Brown LS, Hafner R, John SL, et al: A Controlled Trial of Isoniazid in Persons with Anergy and Human Immunodeficiency Virus Infection Who are at High Risk for Tuberculosis. NEJM 1997;337:315-320.
7. Comstock, GW. Field trials of tuberculosis vaccines: How could we have done better? Controlled Clinical Trials 1994;15:247-276.
8. Colditz GA, Brewer TF, Berkey CS et al. Efficacy of BCG VACCINE in the prevention of tuberculosis. Meta-analysis of the published literature. JAMA 1994;271:698-709.
9. Centers for Disease Control and Prevention. Use of BCG VACCINE in the Control of Tuberculosis. MMWR 43:663-675, 1988.
10. Romanus V: Tuberculosis in bacillus Calmette-Guerin immunized and unimmunized children in Sweden: a ten-year evaluation following the cessation of general bacillus Calmette-Guerin immunization of the newborn in 1975. Pediatr Infect Dis 1987;6:272-280.
11. Smith PG: Case-control studies of the efficacy of BCG against tuberculosis. In: International union against tuberculosis, Proceeding of the XXVIth IUAT World Conference on Tuberculosis and Respiratory Diseases, Singapore. Professional Postgraduate Services, International, Japan, 1987:73-79.
12. Padungchan S, Konjanart S, Kasiratta S, et al: The effectiveness of BCG vaccination of the newborn against childhood tuberculosis in Bangkok. Bull WHO 1986;64:247-258.
13. Tidjani O, Amedone A, ten Dam HG: The protective effect of BCG vaccination of the newborn against childhood tuberculosis in an African community. Tubercle 1986;67:269-281.
14. Young TK, Hershfield ES: A case-control study to evaluate the effectiveness of mass neonatal BCG vaccination among Canadian Indians. Am J Public Health 1986;76:783-786.
15. Shapiro C, Cook N, Evans D, et al.: A case-control study of BCG and childhood tuberculosis in Cali, Columbia. Int J Epidemiol 1985;14:441-446.
16. Rosenthal SR, Loewinsohn E, Graham ML, Liveright D, Throne MG, Johnson V, Baston HC. BCG Vaccination Against Tuberculous in Chicago: a Twenty-year Study Statistically Analyzed. Pediatrics 1961;28:622-641.
17. Data on file, Merck Teknika LLC, Durham, NC, USA.
18. Lorin MI, Hsu KHK, Jacob SC: Treatment of tuberculosis in children. In: Symposium on anti-infective therapy. Pediatric Clinics of North America 1983;30:333-348.
19. Stone MM, Vannier AM, Storch SK, et al.: Brief report: meningitis due to iatrogenic BCG infection in two immunocompromised children. Lancet 1995;333:561-563.
20. Package Insert QuantiFERON®-TB Gold, Cellestis, Inc. July 2010.
21. Package Insert T-SPOT®-TB. Oxford Immunotec Ltd, July 2010.
22. Centers for Disease Control and Prevention. Guidelines for Preventing the Transmission of Mycobacterium Tuberculosis in Health-Care Facilities. MMWR 43:1-38, 1994.
23. Report of the Committee on the Control of Infectious Diseases. American Academy of Pediatrics 1988; 21st Edition.
24. Lotte A, Wazs-Hockert O, Poisson N, Dumitrescu N, Verron M, Couvet E: BCG Complications. Adv Tuberc Res 1984;21:107-193.
25. Mande R: BCG Vaccination. Dawson of Pall Mall, London, UK, 1968, pp. 112-265.
26. Griffith AH: Ten cases of BCG overdose treated with isoniazid. Tubercle 1963;44:247-250.
27. Watkins SM: Unusual complications of BCG vaccination. Brit Med J 1971;1:442.

Manufactured for: Merck Sharp & Dohme LLC
Rahway, NJ 07065, USA

Manufactured by: Merck Teknika LLC, Durham, NC 27712, USA

U.S. License No. 1747

For patent information: www.msd.com/research/patent

TICE is a registered trademark of The Board of Trustees of the University of Illinois, used under the license of Merck Teknika LLC, Durham, NC, USA.

Copyright © 2021-2022 Merck & Co., Inc., Rahway, NJ, USA, and its affiliates.
All rights reserved.

Revised: 08/2022

uspi-v914-pwi-2208r011

BCG VACCINE (for Percutaneous Use) Instructions for Use

Please read this leaflet carefully before administering BCG VACCINE. The vaccine is to be administered after fully explaining the risks and benefits to the vaccinee, parent, or guardian. BCG vaccination should not be given to individuals previously infected with M. tuberculosis. The sterile, single-use multiple puncture device is for use with the BCG VACCINE only.

1. The vaccine should only be administered percutaneously utilizing the supplied sterile, single-use multiple puncture device. Do not inject intravenously, subcutaneously, intramuscularly, or intradermally. The multiple puncture device consists of a plastic holder for a thin, wafer-like stainless steel plate from which 36 points protrude (Figure 1).

Figure 1

2. After the vaccine is prepared, clean the skin site with an alcohol or acetone sponge and allow to dry thoroughly.
3. Administer the vaccine in the deltoid region (Figure 2). Position the arm to maintain a horizontal surface where the vaccine is to be placed.

Figure 2

4. Drop the immunizing dose of 0.2–0.3 mL of BCG VACCINE from the syringe and needle onto the cleansed surface of the skin (Figure 3) and spread over a 1" by 2" area using the smooth edge of the multiple puncture device (Figure 4).

Figure 3

Figure 4

5. Grasp the arm firmly from underneath, tensing the skin. Center the multiple puncture device over the vaccine and apply firm downward pressure such that the device points are well buried in the skin (Figure 5).

Figure 5

6. Maintain pressure for 5 seconds. Do not "rock" the device. Release the pressure underneath the arm and remove the device. In a successful procedure the points puncture the skin. If the points do not puncture the skin, the puncture procedure must be repeated.
7. After successful puncture, spread vaccine as evenly as possible over the puncture area with the smooth edge of the device (Figure 4). An additional 1–2 drops of BCG VACCINE may be added to ensure a very wet vaccination site.
8. Use the multiple puncture device once and discard in a standard biohazardous sharps container.
9. Loosely cover the site and keep dry for 24 hours.
10. Advise the patient that the vaccine contains live organisms. Although the vaccine will not survive in a dry state for long, infection of others is possible.

Caution: Federal law restricts this device to sale by or on the order of a physician.

Multiple puncture devices may be obtained separately from the Order Management Center, Merck Sharp & Dohme LLC, 351 North Sumneytown Pike, North Wales, PA 19454-2505, Telephone number: 800-637-2579.

Manufactured for:
Merck Teknika LLC, Durham, NC 27712, USA

For patent information: www.msd.com/research/patent

Copyright © 2021-2022 Merck & Co., Inc., Rahway, NJ, USA, and its affiliates.
All rights reserved.

Revised:08/2022

ifu-v914-pwi-2208r008

PRINCIPAL DISPLAY PANEL - Vial Carton

NDC 0052-0603-02

BCG
VACCINE

(for Percutaneous Use)

Rx only

Single-Dose Vial